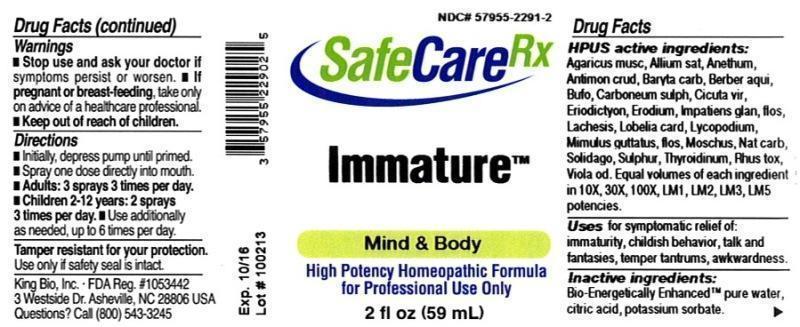 DRUG LABEL: Immature
NDC: 57955-2291 | Form: LIQUID
Manufacturer: King Bio Inc.
Category: homeopathic | Type: HUMAN OTC DRUG LABEL
Date: 20131022

ACTIVE INGREDIENTS: AMANITA MUSCARIA FRUITING BODY 10 [hp_X]/59 mL; GARLIC 10 [hp_X]/59 mL; DILL 10 [hp_X]/59 mL; ANTIMONY TRISULFIDE 10 [hp_X]/59 mL; BARIUM CARBONATE 10 [hp_X]/59 mL; MAHONIA AQUIFOLIUM ROOT BARK 10 [hp_X]/59 mL; BUFO BUFO CUTANEOUS GLAND 10 [hp_X]/59 mL; CARBON DISULFIDE 10 [hp_X]/59 mL; CICUTA VIROSA ROOT 10 [hp_X]/59 mL; ERIODICTYON CALIFORNICUM LEAF 10 [hp_X]/59 mL; ERODIUM CICUTARIUM 10 [hp_X]/59 mL; IMPATIENS GLANDULIFERA FLOWER 10 [hp_X]/59 mL; LACHESIS MUTA VENOM 10 [hp_X]/59 mL; LOBELIA CARDINALIS 10 [hp_X]/59 mL; LYCOPODIUM CLAVATUM SPORE 10 [hp_X]/59 mL; MIMULUS GUTTATUS FLOWERING TOP 10 [hp_X]/59 mL; MOSCHUS MOSCHIFERUS MUSK SAC RESIN 10 [hp_X]/59 mL; SODIUM CARBONATE 10 [hp_X]/59 mL; SOLIDAGO VIRGAUREA FLOWERING TOP 10 [hp_X]/59 mL; SULFUR 10 [hp_X]/59 mL; THYROID, UNSPECIFIED 10 [hp_X]/59 mL; TOXICODENDRON PUBESCENS LEAF 10 [hp_X]/59 mL; VIOLA ODORATA 10 [hp_X]/59 mL
INACTIVE INGREDIENTS: WATER; CITRIC ACID MONOHYDRATE; POTASSIUM SORBATE

Immature™

ACTIVE INGREDIENT

HPUS active ingredients: Agaricus muscarius, Allium sativum, Anethum graveolens, Antimonium crudum, Baryta carbonica, Berberis aquifolium, Bufo rana, Carboneum sulphuratum, Cicuta virosa, Eriodictyon californicum, Erodium, Impatiens glandulifera, flos, Lachesis mutus, Lobelia cardinalis, Lycopodium clavatum, Mimulus guttatus, flos, Moschus, Natrum carbonicum, Solidago virgaurea, Sulphur, Thyroidinum, Rhus toxicodendron, Viola odorata. Equal volumes of each ingredient in 10X, 30X, 100X, LM1, LM2, LM3, LM5 potencies.

INDICATIONS AND USAGE

Uses for symptomatic relief of: immaturity, childish behavior, talk and fantasies, temper tantrums, awkwardness.

Warnings

- Stop use and ask a docter if symptoms persist or worsen.
- If pregnant or breast-feeding, take only on advice of a healthcare professional.

- Keep out of reach of children.

Directions

- Initially, depress pump until primed.
- Spray one dose directly into mouth.
- Adults: 3 sprays 3 times per day.
- Children 2-12 years: 2 sprays 3 times per day.
- Use additionally as needed, up to 6 times per day.

INACTIVE INGREDIENT

Inactive Ingredients: Bio-Energetically Enhanced™ pure water, citric acid and potassium sorbate.

OTHER SAFETY INFORMATION

Tamper resistant for your protection. Use only if safety seal is intact.

PURPOSE

Uses for symptomatic relief of:

- immaturity
- childish behavior
- talk and fantasies
- temper tantrums
- awkwardness